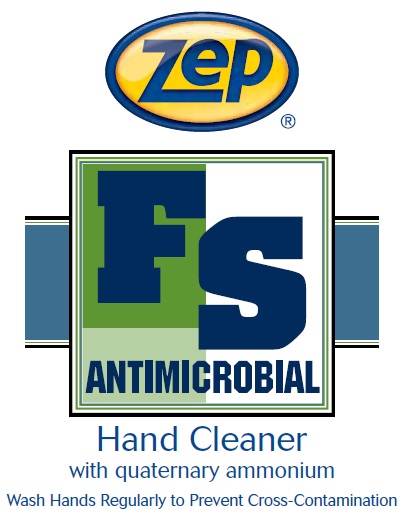 DRUG LABEL: Zep FS Antimicrobial Hand Cleaner
NDC: 66949-105 | Form: LIQUID
Manufacturer: Zep Inc.
Category: otc | Type: HUMAN OTC DRUG LABEL
Date: 20251226

ACTIVE INGREDIENTS: BENZALKONIUM CHLORIDE 0.13 g/100 mL
INACTIVE INGREDIENTS: WATER; PEG-6 COCAMIDE; METHYLISOTHIAZOLINONE; DIDECYLDIMONIUM CHLORIDE; LAURAMINE OXIDE; COCAMIDOPROPYL HYDROXYSULTAINE; METHYLCHLOROISOTHIAZOLINONE; HYDROXYETHYL CELLULOSE (2000 CPS AT 1%); ANHYDROUS CITRIC ACID

66949-105 / 3153 FS Antimicrobial Hand Cleaner

Active ingredient

Benzalkonium chloride 0.13%

Purpose

Antiseptic Hand Wash

Uses

- Hand washing to decrease bacteria on skin.
- For use in food processing facilities.

Warnings

For external use only.

Do not use in the eyes; if in eyes, rinse promptly and thoroughly with water.

When using this product

- Do not swallow.
- If swallowed, do not induce vomiting and if individual is conscious, give large quantities of water to drink and consult a physician immediately.

Stop use and ask a doctor if skin irritation or redness persists for more than 72 hours.

Keep out of reach of children and pets. Children must be supervised in use of this product.

Directions

- Wet hands with water.
- Place hands under dispenser and apply liquid soap.
- Massage soap into hands and wrists, emphasizing back of hands, knuckles, and cuticles.
- Rinse hands thoroughly and dry.

Other information

- Store at 20 to 25°C (68 to 77°F).
- Do not freeze.
- Dispose in accordance with all applicable federal, state and local regulations.

Inactive ingredients

Water, Didecyldimonium Chloride, Cocamidopropyl Hydroxysultaine, Lauramine Oxide, PEG-6 Cocamide, Hydroxyethylcellulose, Methylchloroisothiazolinone and Methylisothiazolinone, Citric Acid

Questions or comments?

Call 1-877-I-BUY-ZEP (1-877-428-9937)